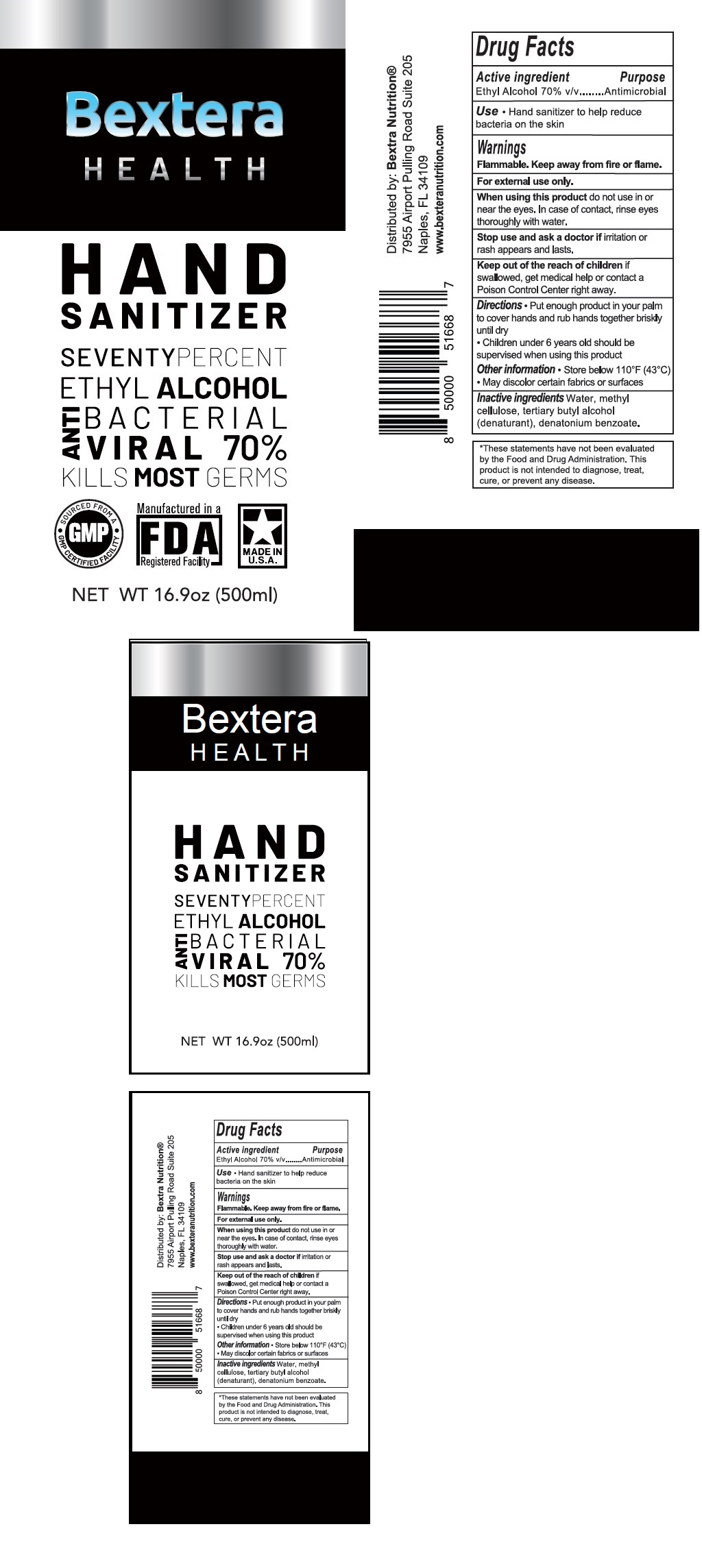 DRUG LABEL: Bextera HEALTH HAND SANITIZER
NDC: 77342-101 | Form: GEL
Manufacturer: Bextera Llc
Category: otc | Type: HUMAN OTC DRUG LABEL
Date: 20200507

ACTIVE INGREDIENTS: ALCOHOL 70 mL/100 mL
INACTIVE INGREDIENTS: WATER; METHYLCELLULOSE, UNSPECIFIED; TERT-BUTYL ALCOHOL; DENATONIUM BENZOATE

Bextera HEALTH HAND SANITIZER

Active ingredient

Ethyl Alcohol 70% v/v

Purpose

Antimicrobial

INDICATIONS AND USAGE

Use • Hand sanitizer to help reduce bacteria on the skin

Warnings

Flammable. Keep away from fire or flame.

For external use only.
When using this product do not use in or near the eyes. In case of contact, rinse eyes thoroughly with water.

Stop use and ask a doctor if irritation or rash appears and lasts.

Keep out of reach of children if swallowed, get medical help or contact a Poison Control Center right away.

DOSAGE AND ADMINISTRATION

Directions • Put enough product in your palm to cover hands and rub hands together briskly until dry

• Children under 6 years old should be supervised when using this product

Other information • Store below 110^0F (43^0C)

• May discolor certain fabrics or surfaces

INACTIVE INGREDIENT

Inactive ingredients Water, methyl cellulose, tertiary butyl alcohol (denaturant), denatonium benzoate.

ANTIBACTERIAL

ANTIVIRAL

KILLS MOST GERMS

SOURCED FROM A GMP CERTIFIED FACILITY

Manufactured in a FDA registered Facility

MADE IN U.S.A

*These statements have not been evaluated by the Food and Drug Administration.

This product is not intended to diagnose, treat, cure, or prevent any disease.

Distributed by: Bextra Nutrition®

7955 Airport Pulling Road Suite 205

Naples, FL 34109

www.bexteranutrition.com